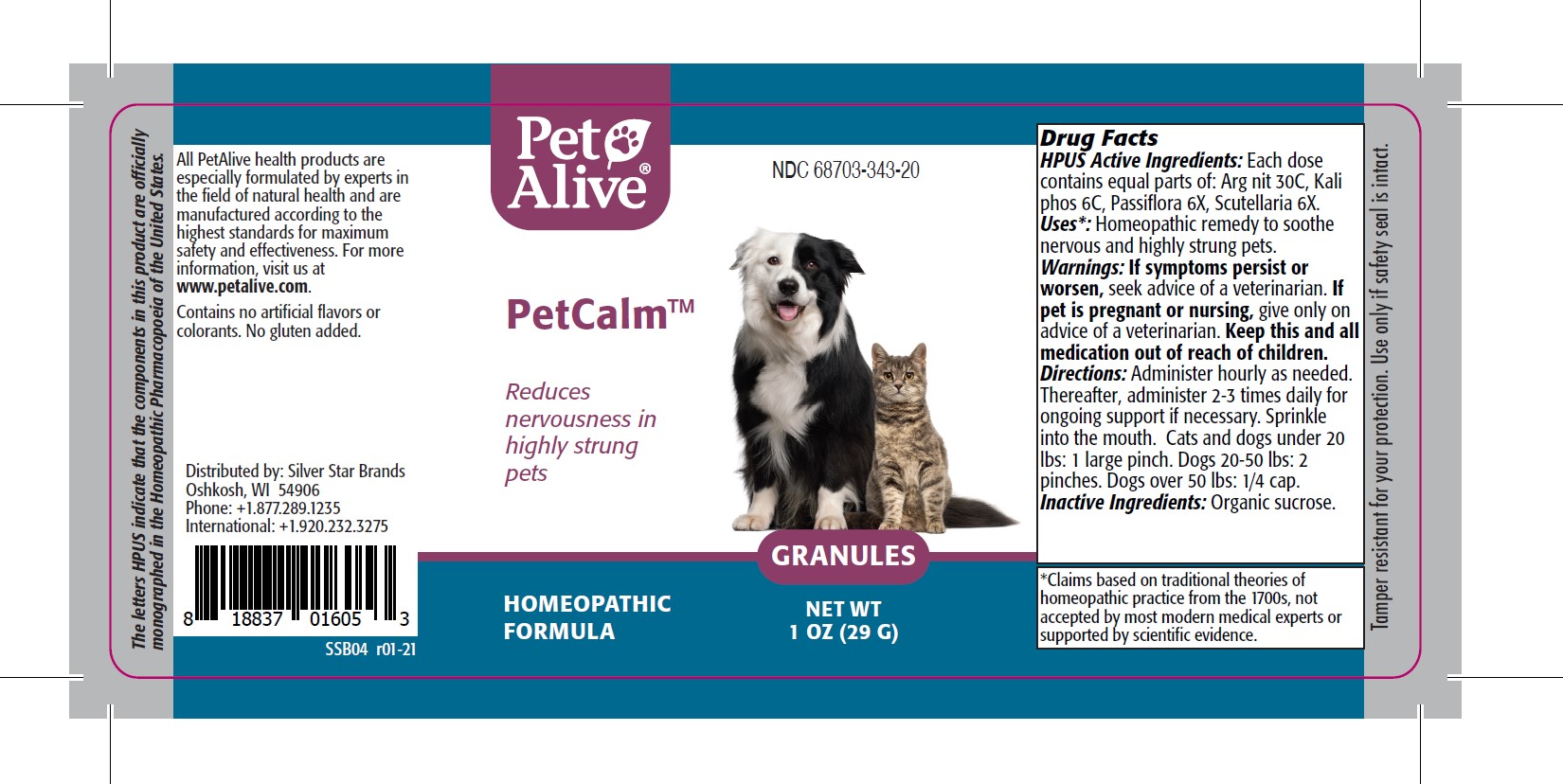 DRUG LABEL: PetAlive PetCalm
NDC: 68703-343 | Form: GRANULE
Manufacturer: SILVER STAR BRANDS
Category: homeopathic | Type: OTC ANIMAL DRUG LABEL
Date: 20251216

ACTIVE INGREDIENTS: SILVER NITRATE 30 [hp_C]/50 mg; POTASSIUM PHOSPHATE, DIBASIC 6 [hp_C]/50 mg; PASSIFLORA INCARNATA FLOWERING TOP 6 [hp_X]/50 mg; SCUTELLARIA LATERIFLORA 6 [hp_X]/50 mg
INACTIVE INGREDIENTS: SUCROSE

PetAlive PetCalm

PURPOSE

Reduces nervousness in highly strung pets.

HPUS Active Ingredients:

Arg nit 30C
Kali phos 6C
Passiflora 6X
Scutellaria 6X

INDICATIONS AND USAGE

Uses: Homeopathic remedy to soothe nervous and highly-strung pets.

WARNINGS

Warnings: If symptoms persist or worsen, seek advice of a veterinarian.

PREGNANCY OR BREAST FEEDING

If pet is pregnant or nursing, give only on advice of a veterinarian.

KEEP OUT OF REACH OF CHILDREN

Keep this and all medication out of reach of children.

DOSAGE AND ADMINISTRATION

Directions: Administer hourly as needed. Thereafter, administer 2-3 times daily for ongoing support if necessary. Sprinkle into the mouth. Cats and dogs under 20 Ibs: 1 large pinch. Dogs 20-50 lbs: 2 pinches. Dogs over 50 lbs: 1/4 cap.

Inactive Ingredients: organic sucrose.

INFORMATION FOR OWNERS/CAREGIVERS

The letters HPUS indicate that the components in this product are officially monographed in the Homeopathic Pharmacopoeia of the United States.

All PetAlive health products are especially formulated by experts in the field of natural health and are manufactured according to the highest standards for maximum safety and effectiveness. For more information, visit us at www.petalive.com.

Contains no artificial flavors or colorants. No gluten added.

Distributed by: Silver Star Brands
Oshkosh, WI 54906
Phone: +1.877.289.1235
International: +1.920.232.3275

STORAGE AND HANDLING

Tamper resistant for your protection. Use only if safety seal is intact.